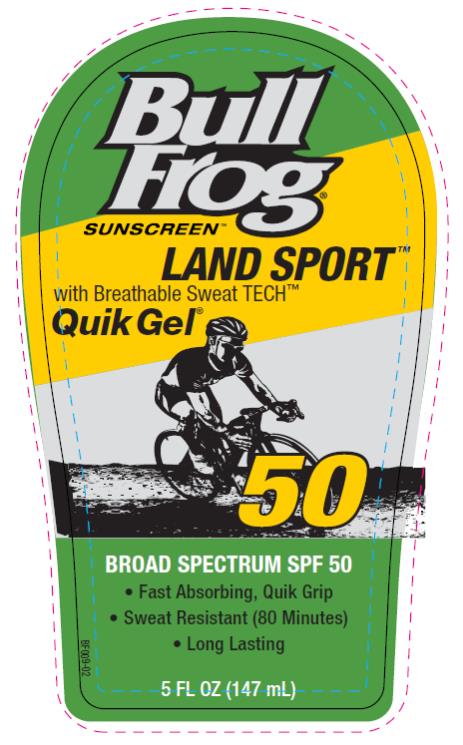 DRUG LABEL: BullFrog SPF50 Land Sport Quik
NDC: 70281-338 | Form: GEL
Manufacturer: SolSkyn Personal Care LLC
Category: otc | Type: HUMAN OTC DRUG LABEL
Date: 20170823

ACTIVE INGREDIENTS: AVOBENZONE 3 mg/100 mg; HOMOSALATE 15 mg/100 mg; OCTISALATE 5 mg/100 mg; OCTOCRYLENE 10 mg/100 mg; OXYBENZONE 6 mg/100 mg
INACTIVE INGREDIENTS: VACHELLIA FARNESIANA FLOWER; .ALPHA.-TOCOPHEROL ACETATE, D-; ALOE VERA LEAF; CAMELLIA OLEIFERA LEAF; CHAMAEMELUM NOBILE FLOWER; CYCLOMETHICONE 6; CYCLOMETHICONE 5; ETHYLHEXYL PALMITATE; GLYCERIN; HYDROXYPROPYL CELLULOSE, UNSPECIFIED; ISOPROPYL MYRISTATE; LAVANDULA ANGUSTIFOLIA SUBSP. ANGUSTIFOLIA FLOWER; PHENETHYL BENZOATE; PPG-12/SMDI COPOLYMER; PROPYLENE GLYCOL; ROSEMARY; ALCOHOL; ALPHA-TOCOPHEROL ACETATE

BullFrog Land Sport Quik Gel SPF 50

BullFrog SPF50 Land Sport Quik Gel

Active Ingredients

Avobenzone 3%, Homosalate 15%, Octisalate 5%, Octocrylene 10%, Oxybenzone 6%

Purpose

Sunscreen

Uses

• helps prevent sunburn

• if used as directed with other sun protection measures (see Directions), decreases the risk of skin cancer and early skin aging caused by the sun

Warnings

• For external use only

• Flammable: keep away from fire or flame.

• Do not use

on damaged or broken skin.

• When using this product

keep out of eyes. Rinse with water to remove.

• Keep out of reach of children.

If product is swallowed, get medical help or contact a Poison Control Center right away.

Directions

• apply liberally 15 minutes before sun exposure

• re-apply:

• after 80 minutes of swimming or sweating

• immediately after towel drying

• at least every 2 hours

Sun Protection Measures. Spending time in the sun increases your risk of skin cancer and early skin aging. To decrease this risk, regularly use a sunscreen with broad spectrum SPF of 15 or higher and other sun protection measures including:

• limit time in the sun, especially from 10 a.m.-2 p.m.

• wear long-sleeved shirts, pants, hats and sunglasses

• children under 6 months: ask a doctor

Other information

• protect this product from excessive heat and direct sun

Inactive Ingredients

Acacia Farnesiana Extract, Acrylates/Octylacrylamide Copolymer, Aloe Barbadensis Leaf Extract, Camellia Oleifera (Green Tea) Leaf Extract, Chamomile Flower Extract, Cyclohexasiloxane, Cyclopentasiloxane, Ethylhexyl Palmitate, Fragrance, Glycerin, Hydroxypropylcellulose, Isopropyl Myristate, Lavender Extract, Phenethyl Benzoate, PPG-12/SMDI Copolymer, Propylene Glycol, Rosemary Leaf Extract, SD Alcohol 40 (50.65% w/w), Tocopheryl (Vitamin E) Acetate

Questions or comments?

www.bullfrogsunscreen.com or call toll-free 1-800-715-3485

MAY STAIN SOME FABRICS, PLASTICS AND WOOD SURFACES.

PRINCIPAL DISPLAY PANEL

Bull
Frog
Sunscreen
Land Sport
Quick Gel
SPF 50